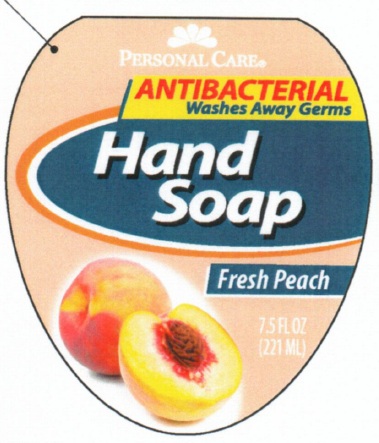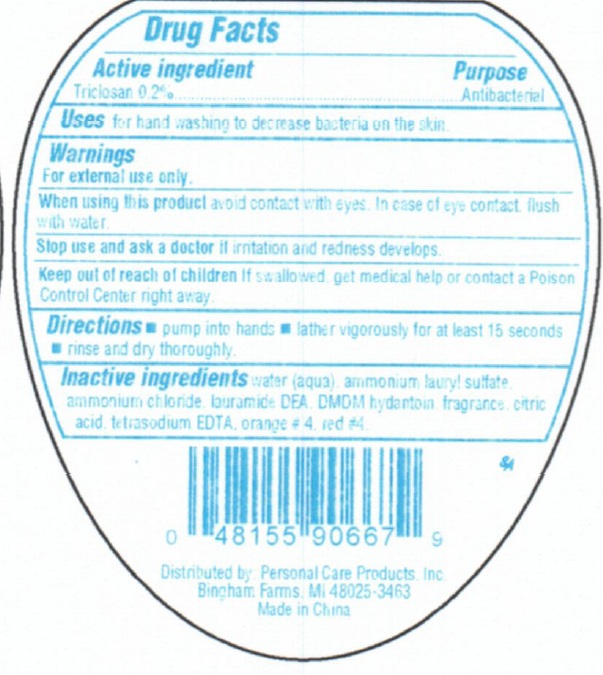 DRUG LABEL: Personal Care Antibacterial Hand - Fresh Peach
                        
NDC: 29500-9078 | Form: SOAP
Manufacturer: Personal Care Products, LLC
Category: otc | Type: HUMAN OTC DRUG LABEL
Date: 20110613

ACTIVE INGREDIENTS: TRICLOSAN 0.2 mL/100 mL
INACTIVE INGREDIENTS: WATER; AMMONIUM LAURYL SULFATE; AMMONIUM CHLORIDE; LAURIC DIETHANOLAMIDE; DMDM HYDANTOIN; CITRIC ACID MONOHYDRATE; EDETATE SODIUM; D&C ORANGE NO. 4; FD&C RED NO. 4

Personal Care Antibacterial Hand Soap - Fresh Peach

Active Ingredient

Triclosan 0.2%

Purpose

Antibacterial

Uses

for handwashing to decrease bacteria on the skin

Warnings

For external use only

When using this product

Avoid contact with eyes. In case of eye contact, flush with water.

Stop use and ask a doctor

if irritation and redness develops

Keep out of reach of children

If swallowed get medical help or contact a Poison Control Center right away.

Directions

pump into hands

lather vigorously for at least 15 seconds

rinse and dry thoroughly

Inactive Ingredients

water (aqua), ammonium lauryl sulfate, ammonium chloride, lauramide DEA, DMDM hydantoin, fragrance, citric acid, tetrasodium EDTA, orange #4, red #4

PACKAGE LABEL

Personal Care

Antibacterial
Washes Away Germs

Hand soap
Fresh Peach 7.5 fl oz
(221ml)
Distributed by Personal Care Products, Inc.
Bingham Farms, MI 48205-3463
Made In China